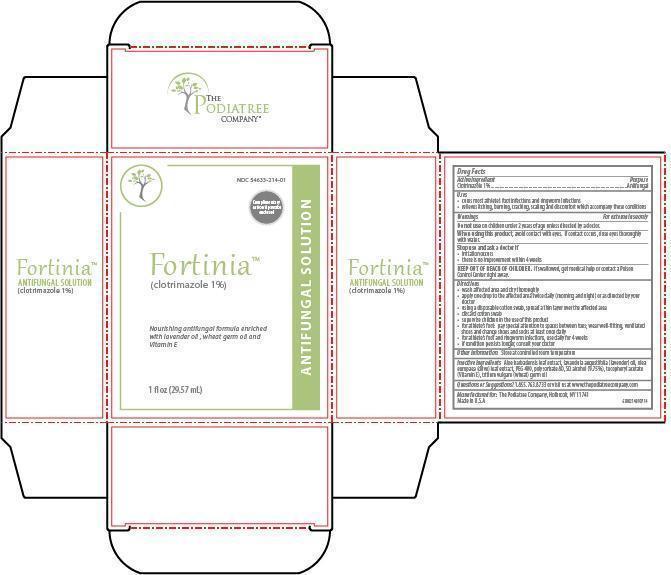 DRUG LABEL: Fortinia
NDC: 54633-214 | Form: SOLUTION
Manufacturer: The Podiatree Company
Category: otc | Type: HUMAN OTC DRUG LABEL
Date: 20260108

ACTIVE INGREDIENTS: CLOTRIMAZOLE 1 g/100 mL
INACTIVE INGREDIENTS: ALOE; LAVENDER OIL; OLEA EUROPAEA LEAF; POLYETHYLENE GLYCOL 400; POLYSORBATE 80; ALCOHOL; .ALPHA.-TOCOPHEROL ACETATE; WHEAT GERM OIL

Active Ingredient

Clotrimazole 1%

Purpose

Antifungal

Uses

• cures most athlete’s foot infections and ringworm infections
• relieves itching, burning, cracking, scaling and discomfort which accompany these conditions

Warnings

For external use only

Do not use

on children under 2 years of age unless directed by a doctor.
When using this product, avoid contact with eyes. If contact occurs, rinse eyes thoroughly with water.

Stop use and ask a doctor or pharmacist if

• irritation occurs
• there is no improvement within 4 weeks

KEEP OUT OF REACH OF CHILDREN.

In case of accidental ingestion, seek medical help or contact a Poison Control Center immediately.

Directions

• wash affected area and dry thoroughly
• apply one drop to the affected area twice daily (morning and night) or as directed by your doctor
• using a disposable cotton swab, spread a thin layer over the affected area
• discard cotton swab
• supervise children in the use of this product
• for athlete’s foot: pay special attention to spaces between toes; wear well-fitting, ventilated shoes and change shoes and socks at least once daily
• for athlete’s foot and ringworm infections, use daily for 4 weeks
• this product is not effective on scalp or nails

Other Information

Store at controlled room temperature.

Inactive Ingredients

Aloe barbadensis leaf extract, lavandula augustifolia (lavender) oil, olea europaea (olive) leaf extract, PEG 400, polysorbate 80, SD alcohol (9.75%), tocopheryl acetate (Vitamin E), tritium vulgare (wheat) germ oil

Questions or Suggestions?

1.855.763.8733 or visit us at www.thepodiatreecompany.com

PRINCIPAL DISPLAY PANEL

Label